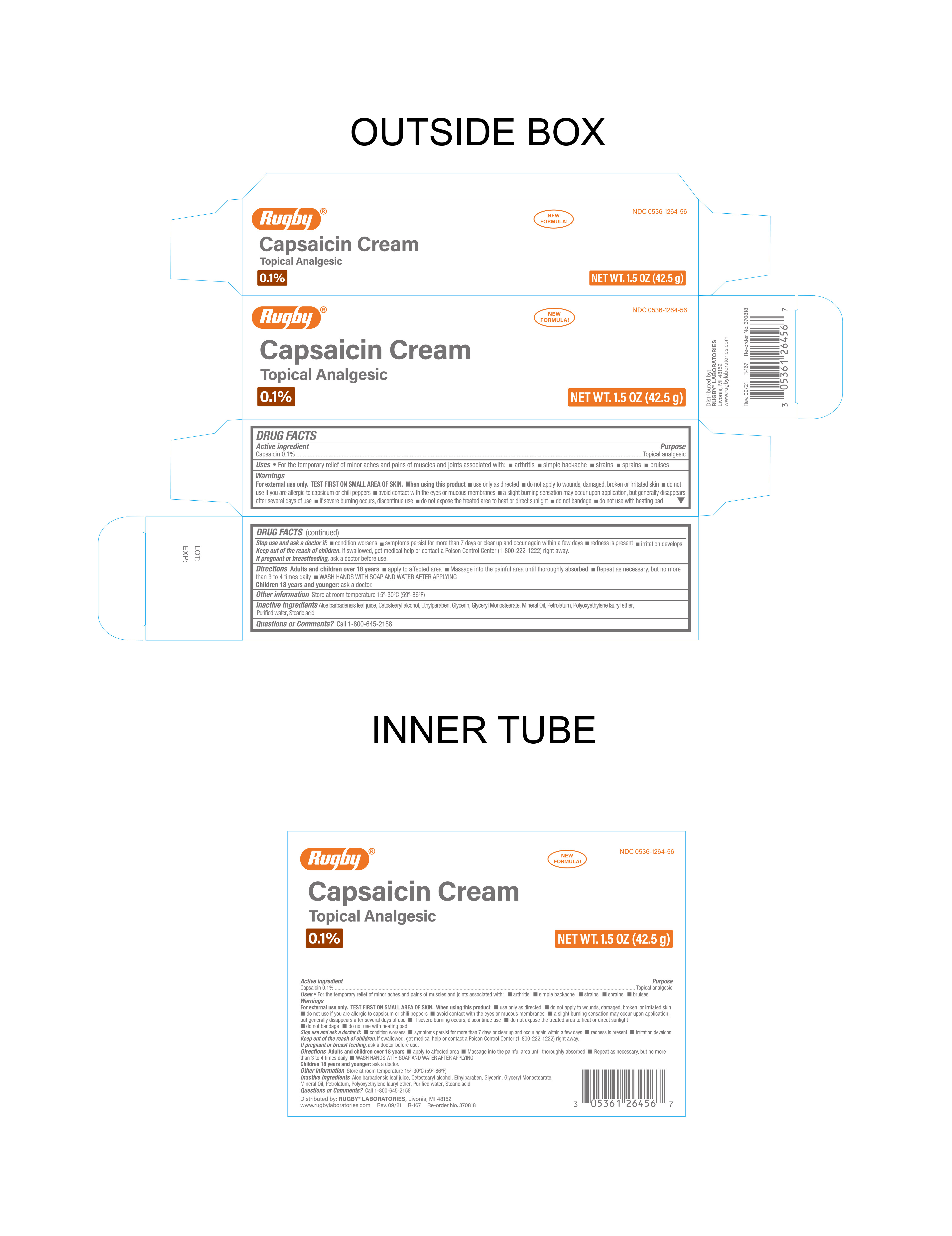 DRUG LABEL: Rugby Capsaicin Cream
NDC: 0536-1264 | Form: CREAM
Manufacturer: Rugby Laboratories
Category: otc | Type: HUMAN OTC DRUG LABEL
Date: 20251202

ACTIVE INGREDIENTS: CAPSAICIN 0.1 g/100 g
INACTIVE INGREDIENTS: ALOE VERA LEAF; ETHYLPARABEN; MINERAL OIL; STEARYL ALCOHOL; WATER; GLYCERIN; GLYCERYL MONOSTEARATE; PETROLATUM; LAURETH-15; CETOSTEARYL ALCOHOL

Rugby Capsaicin Cream

Active Ingredient

Capsaicin 0.1%

Purpose

Topical Analgesic

Warnings

For external use only: TEST FIRST ON SMALL AREA OF SKIN.

When using this product:

- Use only as directed
- Do not apply to wounds, damaged, broken or irritated sin
- Do not use if you are allergic to capssicum or chili peppers
- Avoid contact with the eyes or mucous membranes
- A slight burning sensation may occur upon application, but generally disappears after several days of use
- If severe burning occurs, discontinue use
- Do not expose the treated area to heat or direct sunlight
- Do not bandage
- Do not use with heating pad

Stop Use and Ask Doctor if:

- Condition worsens
- Symptoms persist for more than 7 days or clear up and occur again within a few days
- Redness is present
- irritation develops

Keep Out of the Reach of Children

If swallowed, get medical help or contact a Poison Control Center (1-800-222-1222) right away.

Uses

For the temporary relief of minor aches and pains of muscles and joints associated with:

- Arthritis
- Simple Backache
- Strains
- Sprains
- Bruises

If Pregnant or Breast Feeding

Ask a doctor before use

Directions

Adults and Children over 18 years:

- Apply to affected area
- Massage into the painful area until thoroughly absorbed
- Repeat as necessary but not more than 3 to 4 times daily
- WASH HANDS WITH SOAP AND WATER AFTER APPLYING

Children 18 years and younger:

Ask a doctor

Inactive Ingredients

Aloe barbadensis leaf juice, Cetostearyl alcohol, Ethylparaben, Glycerin, Glyceryl monostearate, Mineral Oil, Petrolatum, Polyoxyethylene lauryl ether, Purified Water, stearic acid.

Questions

Call 1-800-645-2158

Distributed By:

RUGBY®LABORATORIES

Livonia, MI 48152

www.rugbylaboratories.com

rev. 09/21 R-167 Re-order No. 370818

Other Information

Store at room temperature 15°-30°F (59°-86°F)